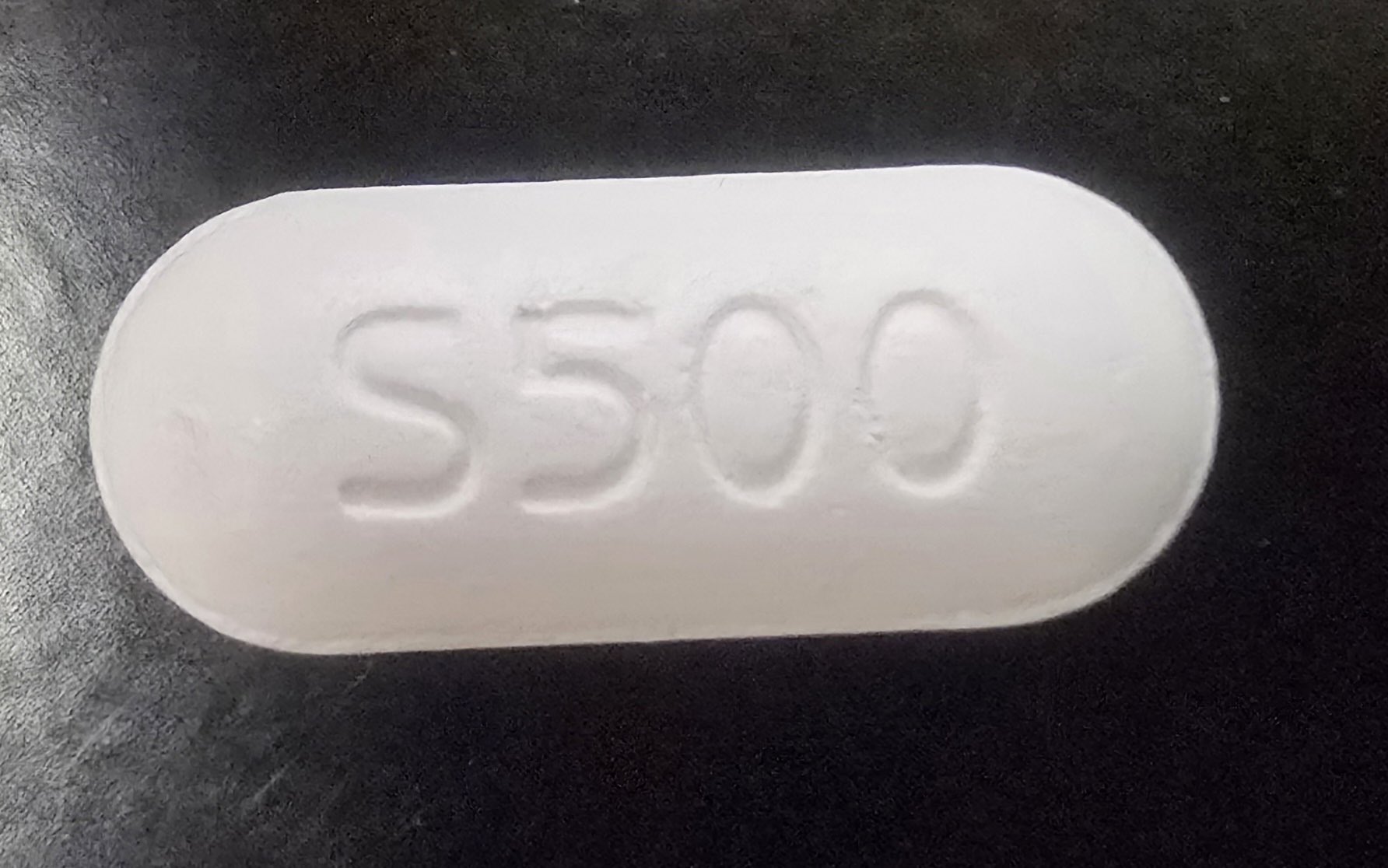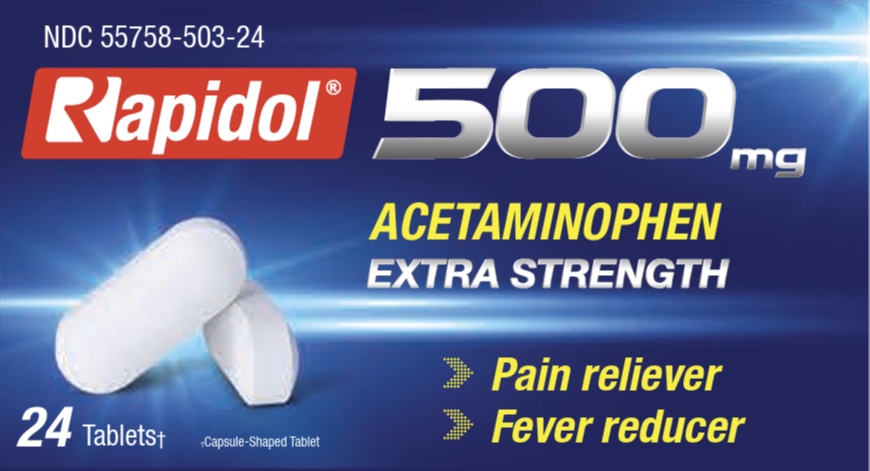 DRUG LABEL: Rapidol
NDC: 55758-503 | Form: CAPSULE, COATED
Manufacturer: Pharmadel LLC
Category: otc | Type: HUMAN OTC DRUG LABEL
Date: 20250730

ACTIVE INGREDIENTS: ACETAMINOPHEN 500 mg/1 1
INACTIVE INGREDIENTS: TITANIUM DIOXIDE; STARCH, CORN; HYPROMELLOSE, UNSPECIFIED; MAGNESIUM STEARATE; POLYETHYLENE GLYCOL, UNSPECIFIED; POVIDONE; STEARIC ACID; MICROCRYSTALLINE CELLULOSE; TALC

Rapidol Acetaminophen 500 (HHH)

Drug Facts

.

Active ingredient & Purposes

Active ingredient (in each tablet) | Purposes
Acetaminophen 500 mg | Pain reliever/ fever reducer

Uses

For the temporary relief of minor aches and pains due to:

- the common cold
- headache
- backache
- muscular aches
- toothache
- minor pain of arthritis
- premenstrual and menstrual cramps
- temporarily reduces fever

Warnings

Liver warning:This product contains acetaminophen. Severe liver damage may occur if you take

- more than 6 tablets in 24 hours, which is the maximum daily amount
- with other drugs containing acetaminophen
- 3 or more alcoholic drinks every day while using this product

Allergy alert:acetaminophen may cause severe skin reactions. Symptoms may include:

■ skin reddening

■ blisters

■ rash

If a skin reaction occurs, stop use and seek medical help right away.

Do not use

- with any other drug containing acetaminophen (prescription or nonprescription). If you are not sure whether a drug contains acetaminophen, ask a doctor or pharmacist.
- If allergic to of the inactive ingredients in this product

Ask a doctor before use if you have

liver disease

Ask a doctor or pharmacist before use if you are

taking the blood thinning drug warfarin

Stop use and ask a doctor if

- pain gets worse or lasts more than 10 days
- fever gets worse or lasts more than 3 days
- redness or swelling is present
- any new symptoms occur

These could be signs of a serious condition.

If pregnant or breast feeding,

ask a health professional before use.

Keep out of reach of children.

In case of overdose, get medical help or contact a Poison Control Center right away. Prompt medical attention is critical for adults as well as for children even if you do not notice any signs or symptoms.

Directions

Age | Dose
adults and children 12 years of age and older | - take 2 tablets every 6 hours while symptoms last. - do not take more than 6 tablets in 24 hours, unless directed by a doctor
children under 12 years of age | - consult a doctor

Other information

- store between 77-86°F (25-30°C)

Inactive ingredients

corn starch, hypromellose, magnesium stearate, microcrystalline cellulose, polyethylene glycol, povidone, stearic acid, talc, titanium dioxide

Dist. by/ por:

PHARMADEL LLC

New Castle, DE 19720

+1-866-359-3478